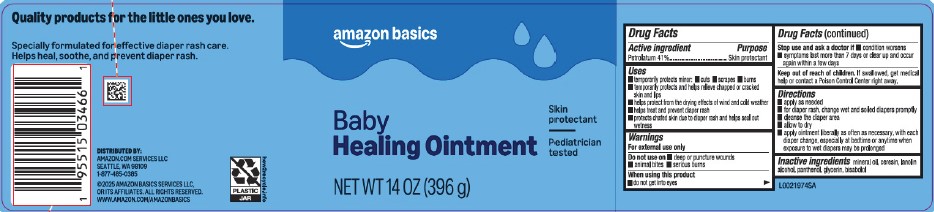 DRUG LABEL: Petrolatum
NDC: 72288-180 | Form: OINTMENT
Manufacturer: Amazon.com Services LLC
Category: otc | Type: HUMAN OTC DRUG LABEL
Date: 20250915

ACTIVE INGREDIENTS: PETROLATUM 410 mg/1 g
INACTIVE INGREDIENTS: MINERAL OIL; CERESIN; LANOLIN ALCOHOLS; PANTHENOL; GLYCERIN; LEVOMENOL

Basics 180.000/180AC
Healing Ointment for Babies

Active ingredient

Petrolatum 41%

Purpose

Skin protectant

Uses

- temporarily protects minor: cuts - scrapes - burns
- temporarily protects and helps relieve chapped or cracked skin and lips
- helps protect from the drying effects of wind and cold weather
- helps treat and prevent diaper rash
- protects chafed skin due to diaper rash and helps seal out wetness

Warnings

For external use only

Do not use on

- deep or puncture wounds
- animal bites
- serious burns

When using this product

do not get into eyes

Stop use and ask a doctor if

- condition worsens
- symptoms last more than 7 days or clear up and occur again within a few days

Keep out of the reach of children.

If swallowed, get medical help or contact a Poison control Center right away.

Directions

- apply as needed
- for diaper rash, change wet and soiled diapers promptly
- cleanse the diaper area
- allow to dry
- apply ointment liberally as often as necessary, with each diaper change, especially at bedtime or anytime when exposure to wet diapers may be prolonged

Inactive ingredients

mineral oil, ceresin, lanolin alcohol, panthenol, glycerin, bisabolol

Claims

Quality products for the little ones you love.

Specially formulated for effective diaper rash care.

Helps heal, soothe, and prevent diaper rash.

Adverse reaction

DISTRIBUTED BY:

Amazon.com Services LLC

Seattle, WA 98109

1-877-485-0385

amazon

© 2025 Amazon Basics Services LLC, or its affiliates.

All rights reserved.

www.amazon.com/amazonbasics

PLASTIC JAR

how2recycle.info

principal dispay panel

amazon basics

baby

healing ointment

Skin Protectant

Pediatrician Tested

NET WT 14 OZ (396 g)